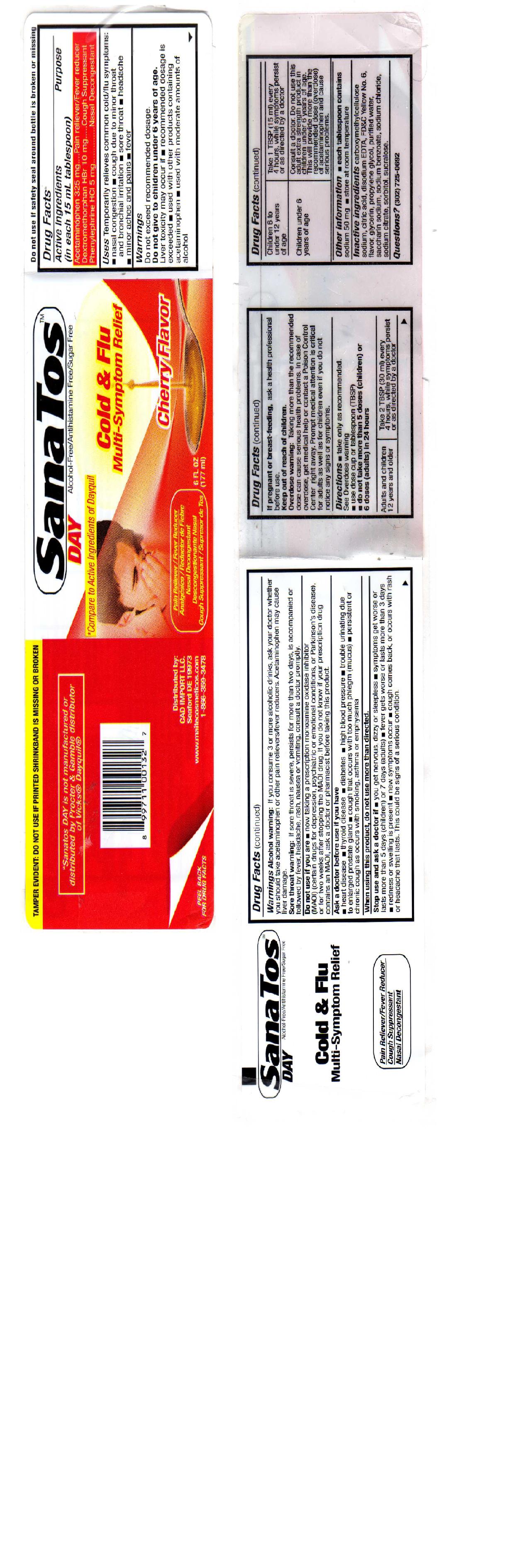 DRUG LABEL: Sanatos
NDC: 14505-398 | Form: LIQUID
Manufacturer: Pharmalab Enterprises Inc
Category: otc | Type: HUMAN OTC DRUG LABEL
Date: 20100909

ACTIVE INGREDIENTS: ACETAMINOPHEN 325 mg/15 mL; DEXTROMETHORPHAN HYDROBROMIDE 10 mg/15 mL; PHENYLEPHRINE 5 mg/15 mL
INACTIVE INGREDIENTS: CARBOXYMETHYLCELLULOSE SODIUM; CITRIC ACID MONOHYDRATE; EDETATE DISODIUM; FD&C YELLOW NO. 6; GLYCERIN; PROPYLENE GLYCOL; WATER; SACCHARIN SODIUM; SODIUM BENZOATE; SODIUM CHLORIDE; SODIUM CITRATE; SORBITOL; SUCRALOSE

Drug Facts

Active Ingredients Purpose
(in each 15 mL tablespoon)
Acetaminophen 325m........ Pain Reliever/Fever Reducer
Dextromethorphan HBr 10mg...... Cough Suppressant
Phenylephrine HCl 5mg..................Nasal Decongestant

PURPOSE

Uses: Temporarily relieves common cold/flu symptoms:

- Nasal Congestion
- Cough due to Minor Throat and Bronchial Irritation
- Sore Throat
- Headache
- Minor Aches and Pains
- Fever

Warnings: Do not exceed recommended dosage.
Do not give to children under 12 years of age.
Liver Toxicity may occur if:

- Recommended dosage is exceeded
- Used with other products containing acetaminophen
- Used with moderate amounts of alcohol

Alcohol Warning: If you consume 3 or more alcoholic drinks, ask your doctor whether you should take acetaminophen or other pain relievers. Acetaminophen may cause liver damage.
Sore Throat Warning: If sore throat is severe, persists for more than two days, is accompanied or followed by fever, headache, rash, nausea or vomiting, consult a doctor promptly.

Do not use if you are:

- now taking a prescription monoamine oxidase inhibitor(MAOI) (certain drugs for depression, psychiatric or emotional conditions, or Parkinson's disease), or for two weeks after stopping the MAOI drug. If yuo do not know if your prescription drug contains an MAOI, ask a doctor or pharmacist before taking this product

Ask a doctor before use if you have:

- Heart Disease
- Thyroid Disease
- Diabetes
- High Blood Pressure
- Trouble urinating due to enlarged prostate gland
- Cough that occurs with too much phlegm(mucus)
- Persistent or chronic cough as occurs with smoking, asthma or emphysema

When using this product, do not use more than directed

Stop Use and ask a doctor if:

- you get nervous, dizzy, or sleepless
- symptoms get worse or lasts more than 5 days(children) or 7 days (adults)
- fever gets worse or lasts more than 3 days
- redness or swelling is present
- new symptoms occur
- cough comes back, or occurs with rash or headache that lasts. This could be signs of a serious condition.

PREGNANCY OR BREAST FEEDING

If pregnant of breast-feeding, ask a health professional before use.

Keep out of reach of children.

OVERDOSAGE

Overdose warning: Taking more than the recommended dose can cause serious health problems. In case of overdose, get medical help or contact a Poison Control Center right away. Prompt medical attention is critical for adults as well as for children even if you do not notice any signs or symptoms.

Directions:

- take only as recommended.

See Overdose warning.

- use dose cup or tablespoon(TBSP)
- do not use more than 5 doses(children) or 6 doses(adults) in 24 hours

Adults and children 12 years and older: Take 2 TBSP(30ml) every 4 hours, while symptoms persist or as directed by a doctor
Children 6 to under 12 years of age: take 1 TBSP 15ml every 4 hours, while symptoms persist or as directed by a doctor
Children under 6 years of age: Consult a doctor. Do not use this adult extra strength product in children under 6 years of age. This will provide more than the recommended dose(overdose) of acetaminophen and cause serious problems.

Other information: each tablespoon contains sodium 50 mg

Questions? (302) 725-0692